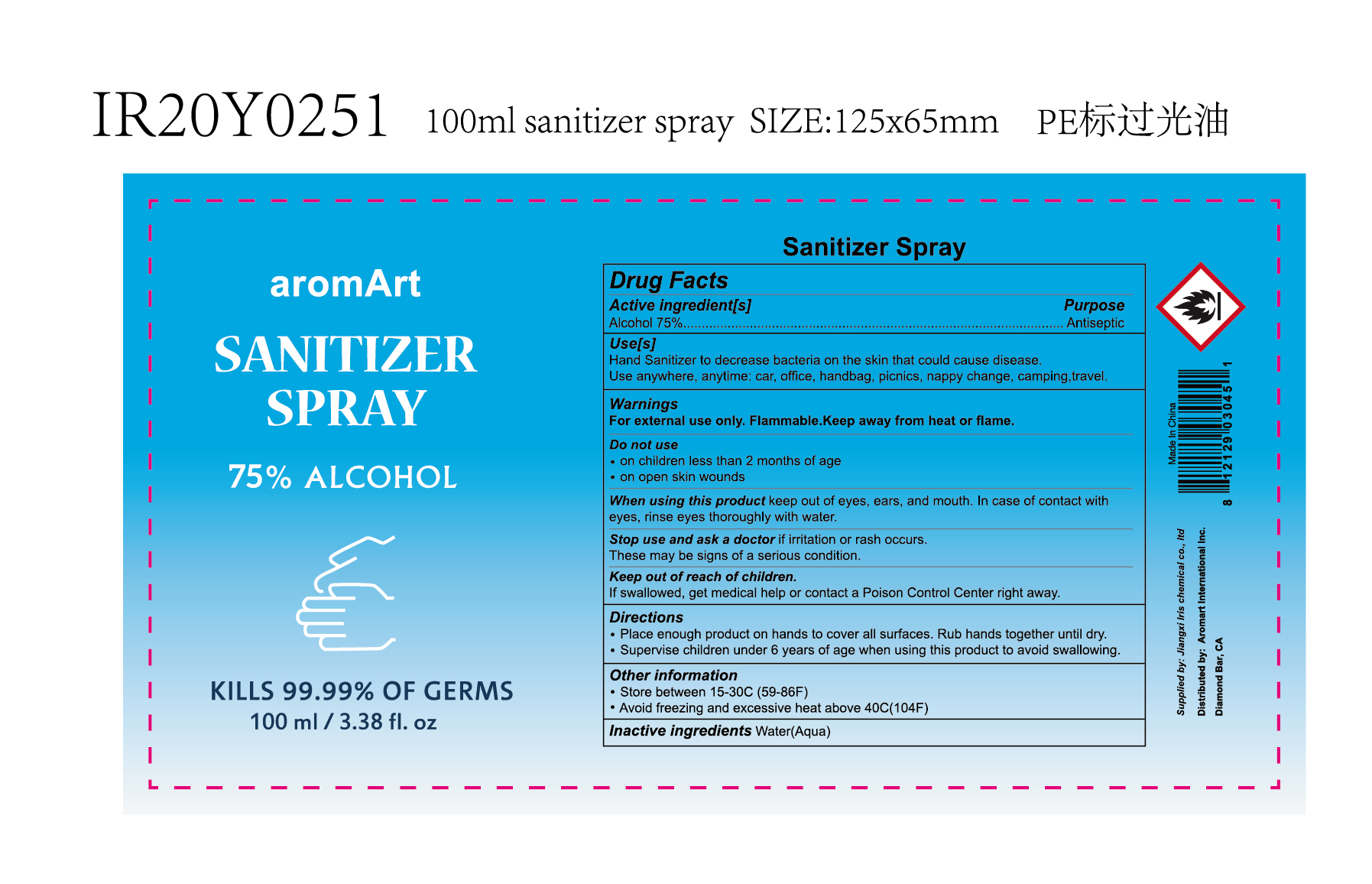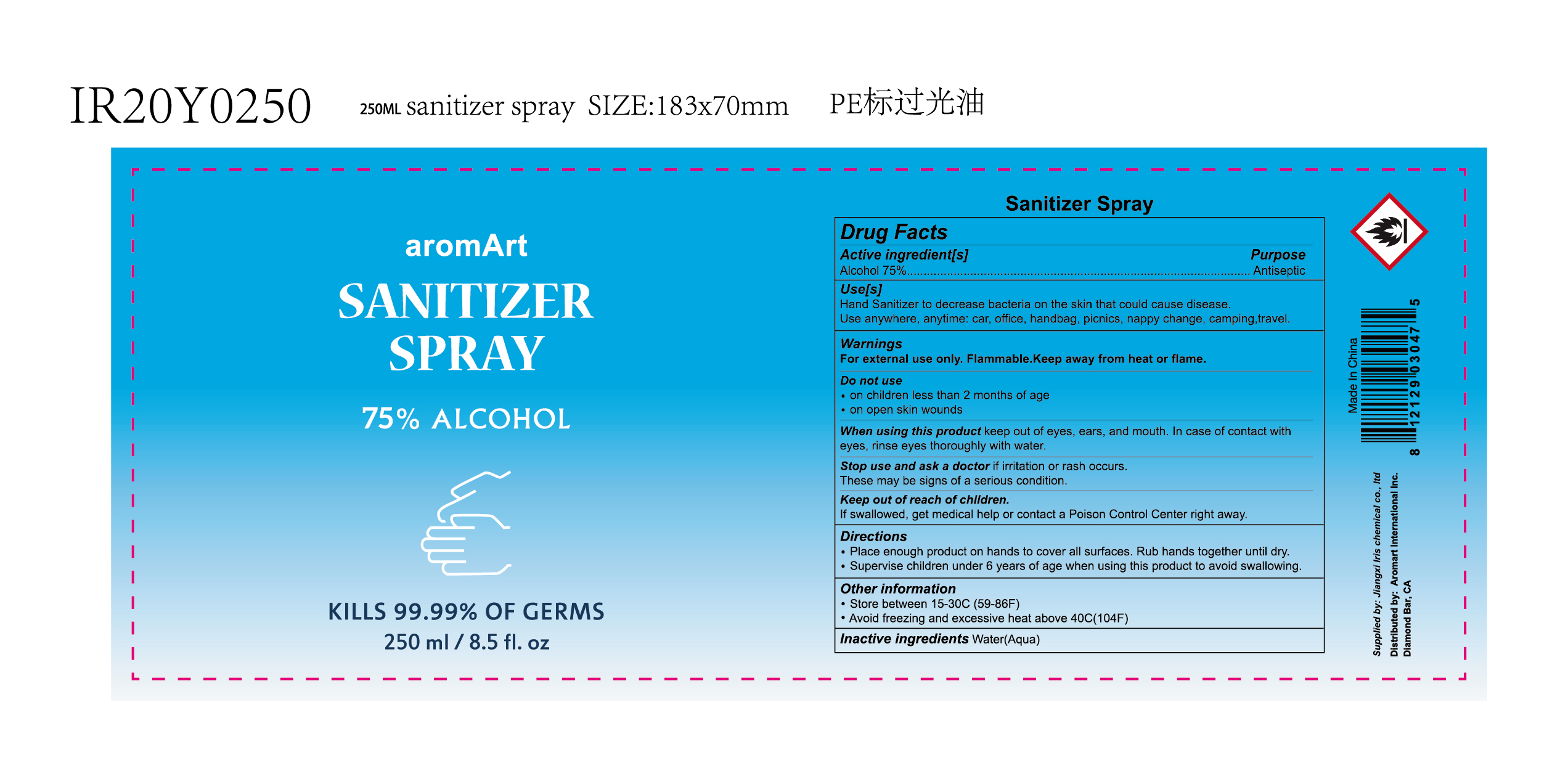 DRUG LABEL: SANITIZER
NDC: 74440-006 | Form: SPRAY
Manufacturer: Jiangxi Iris Chemical Co.,Ltd
Category: otc | Type: HUMAN OTC DRUG LABEL
Date: 20200521

ACTIVE INGREDIENTS: ALCOHOL 75 mL/100 mL
INACTIVE INGREDIENTS: WATER

SANITIZER SPRAY

Active ingredient[s]

Alcohol 75%.

Purpose

Antiseptic

Use[s]

Hand Sanitizer to decrease bacteria on the skin that could cause disease.

Use anywhere,anytime;car, office,handbag,picnics,nappy change,camping,travel.

Warnings

For external use only.Flammable.Keep away from heat or flame.

Do not use

on children less than 2 months of age

on open skin wounds

When using this product

keep out of eyes,ears,and mouth.In case of contact with eyes, rinse eyes thoroughly with water.

Stop use and ask a doctor

if irritation or rash occurs.

These may be signs of a serious condition.

Keep out of reach of children

If swallowed, get medical help or contact a Poison Control Center right away.

Directions

Place enough product on hands to cover all surfaces.Rub hands together until dry.

Supervise children under 6 years of age when using this product to avoid swallowing.

Other information

Store between 15-30C(59-86F)

Avoid freezing and excessive heat above 40C(104F)

Inactive ingredients

Water(Aqua)